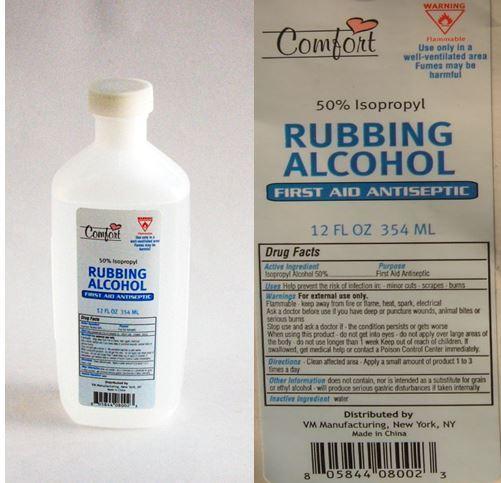 DRUG LABEL: Comfort
NDC: 50827-002 | Form: LIQUID
Manufacturer: WEIMEI Lianyungang HOUSEHOLD ARTICLES MANUFACTURING CO.LTD
Category: otc | Type: HUMAN OTC DRUG LABEL
Date: 20140103

ACTIVE INGREDIENTS: ISOPROPYL ALCOHOL 50 mL/100 mL
INACTIVE INGREDIENTS: Water

Active Ingredient

Isopropyl Alcohol 50%

Purpose

First Aid Antiseptic

Uses

Help Prevent the risk of infection in Minor Cuts - Scrapes - Burns

Warnings

For External Use Only

Flammable - Keep away from fire or flame, heat, spark, electrical

Ask a doctor before use if ou have deep or punture wound, animal bites or serious burns

Stop use and ask doctor if the condition persisits or gets worse

When using this product, do not get into eyes do not apply over large areas of the body

do not use longer than a week

Keep out of reach of children. If swallowed, get medical help or contact a posion control center immediately

Directions

Clean affected area - apply a small amount of product 1 to 3 times a day

Other Information

does not contain nor is intened as substitute for grain or ethyl alcohol. will produce serious gastric disturbances if taken internally

Inactive Ingredient

Water

Package Label

Alcohol